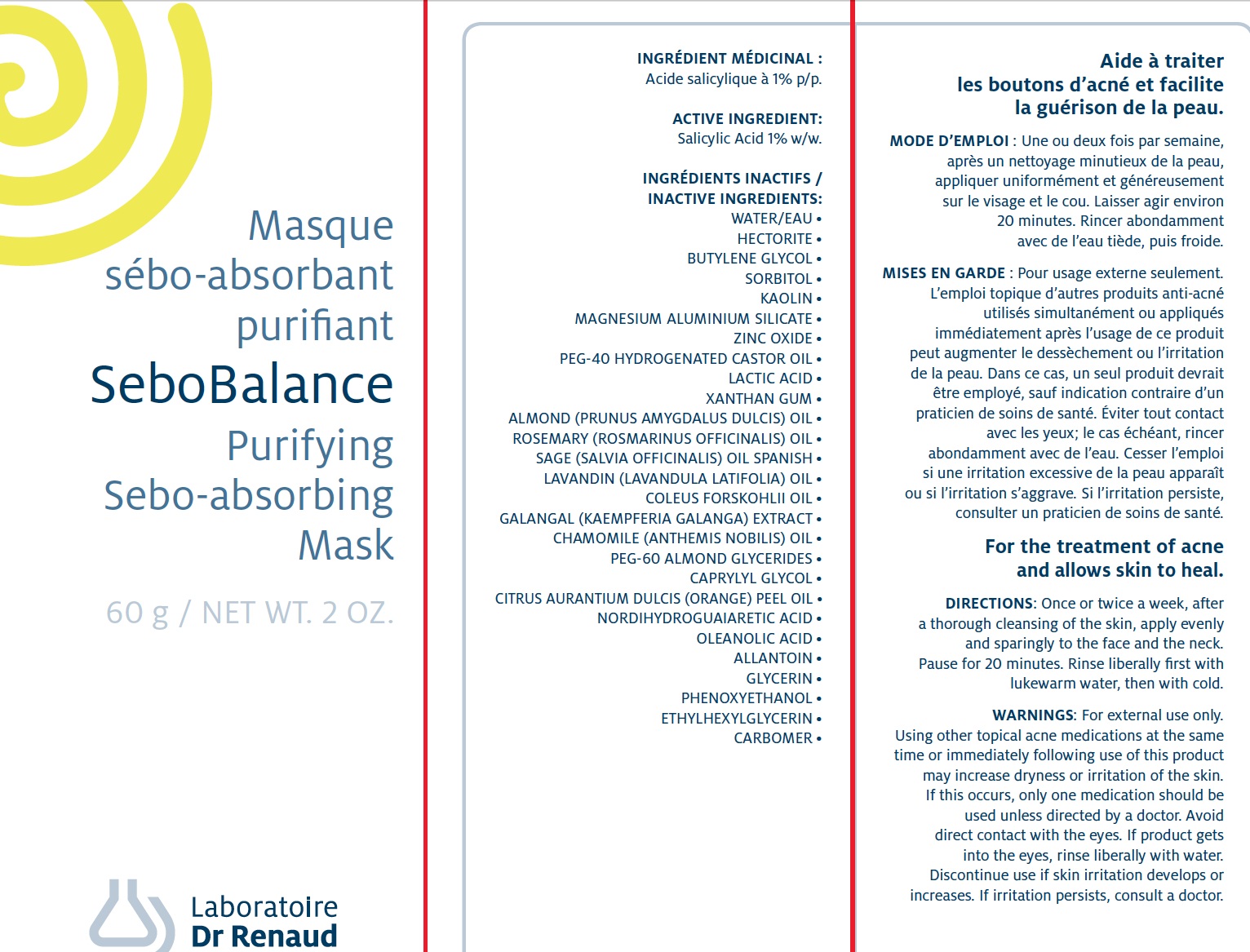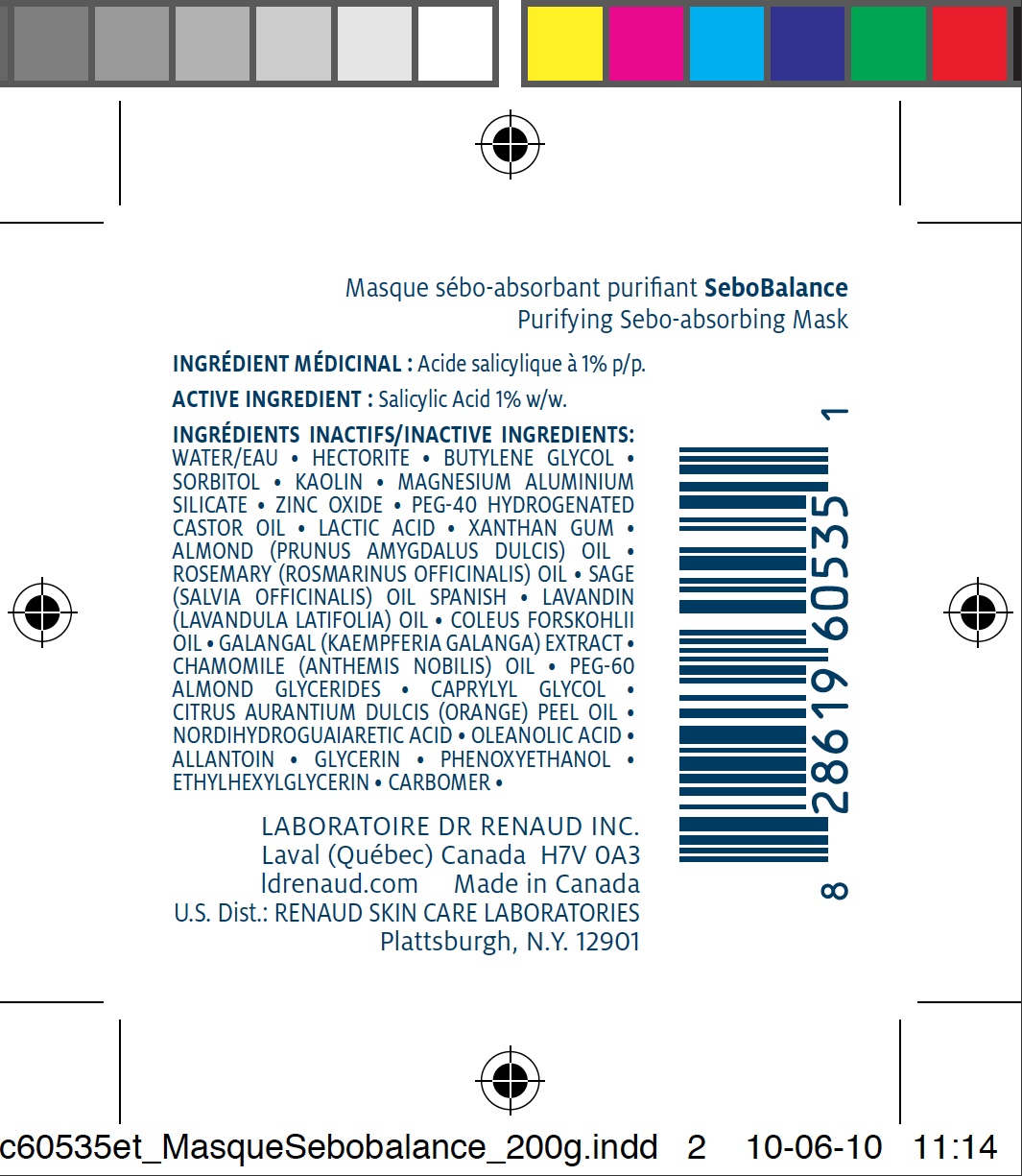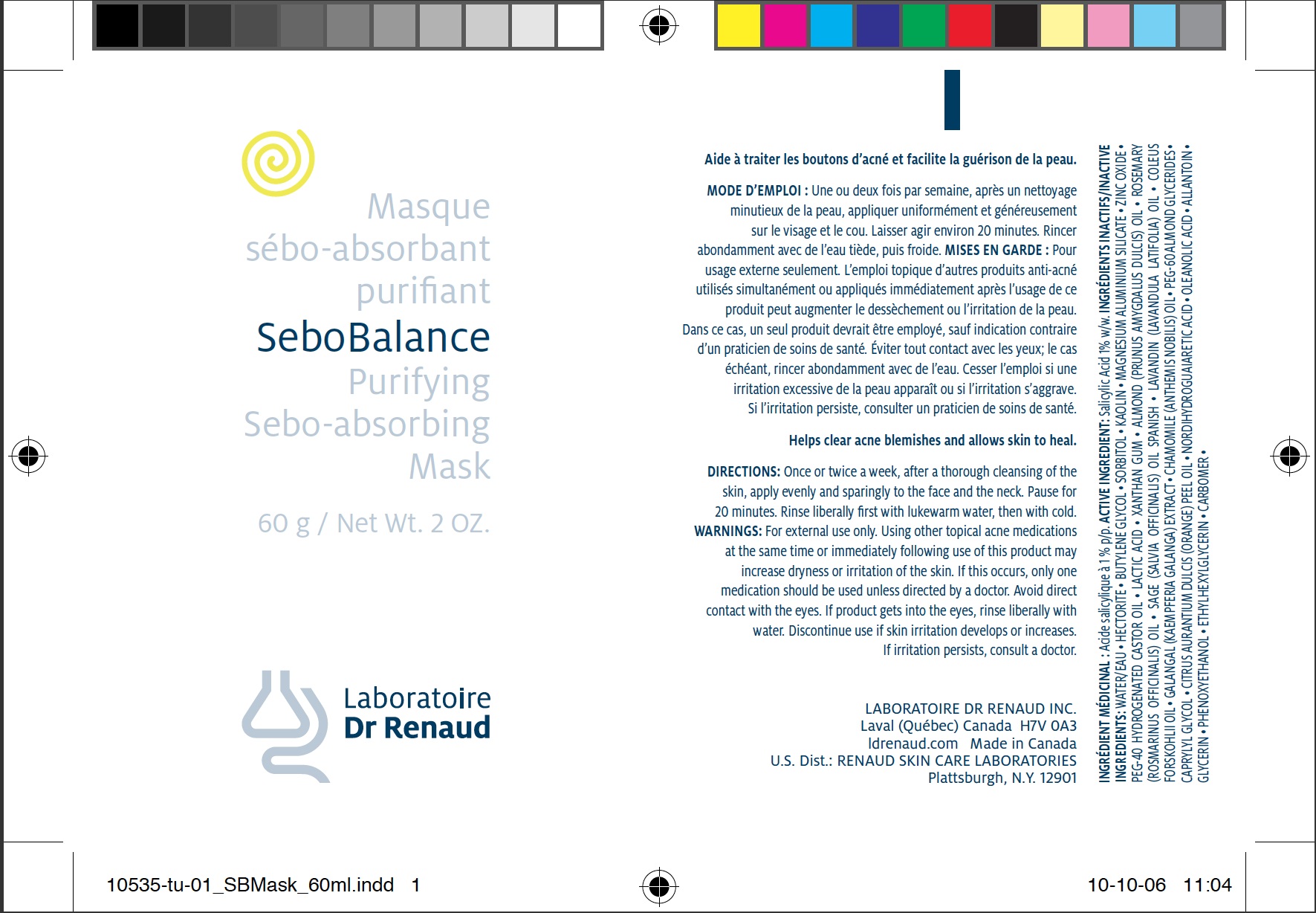 DRUG LABEL: SEBOBALANCE Purifying Sebo-absorbing Mask
NDC: 62499-535 | Form: PASTE
Manufacturer: Laboratoire Dr. Renaud
Category: otc | Type: HUMAN OTC DRUG LABEL
Date: 20100629

ACTIVE INGREDIENTS: SALICYLIC ACID 1 g/100 g
INACTIVE INGREDIENTS: WATER; HECTORITE; BUTYLENE GLYCOL; SORBITOL; KAOLIN; MAGNESIUM ALUMINUM SILICATE; ZINC OXIDE; HYDROGENATED CASTOR OIL; LACTIC ACID; XANTHAN GUM; PHENOXYETHANOL; ALMOND OIL; ROSEMARY OIL; SAGE OIL; LAVANDIN OIL; GALANGAL OIL; CHAMOMILE FLOWER OIL; CAPRYLYL GLYCOL; ORANGE OIL; ALLANTOIN; GLYCERIN; ETHYLHEXYLGLYCERIN; CARBOMER 934; MASOPROCOL; OLEANOLIC ACID

Drug Facts

ACTIVE INGREDIENT

Salicylic Acid 1% w/w.

INACTIVE INGREDIENTS

WATER/EAU • HECTORITE • BUTYLENE GLYCOL • SORBITOL • KAOLIN • MAGNESIUM ALUMINIUM SILICATE • ZINC OXIDE • PEG-40 HYDROGENATED CASTOR OIL • LACTIC ACID • XANTHAN GUM • ALMOND (PRUNUS AMYGDALUS DULCIS) OIL • ROSEMARY (ROSMARINUS OFFICINALIS) OIL • SAGE (SALVIA OFFICINALIS) OIL SPANISH • LAVANDIN (LAVANDULA LATIFOLIA) OIL • COLEUS FORSKOHLII OIL • GALANGAL (KAEMPFERIA GALANGA) EXTRACT • CHAMOMILE (ANTHEMIS NOBILIS) OIL • PEG-60 ALMOND GLYCERIDES • CAPRYLYL GLYCOL • CITRUS AURANTIUM DULCIS (ORANGE) PEEL OIL • NORDIHYDROGUAIARETIC ACID • OLEANOLIC ACID • ALLANTOIN • GLYCERIN • PHENOXYETHANOL • ETHYLHEXYLGLYCERIN • CARBOMER •

PURPOSE

For the treatment of acne and allows skin to heal.

DIRECTIONS

Once or twice a week, after
a thorough cleansing of the skin, apply evenly
and sparingly to the face and the neck.
Pause for 20 minutes. Rinse liberally first with
lukewarm water, then with cold.

WARNINGS

For external use only.
Using other topical acne medications at the same
time or immediately following use of this product
may increase dryness or irritation of the skin.
If this occurs, only one medication should be
used unless directed by a doctor. Avoid
direct contact with the eyes. If product gets
into the eyes, rinse liberally with water.
Discontinue use if skin irritation develops or
increases. If irritation persists, consult a doctor.

image of carton 60g label
image of tube 200g label
image of tube 60g label

INDICATIONS AND USAGE

Enter section text here

Keep out of reach of children.